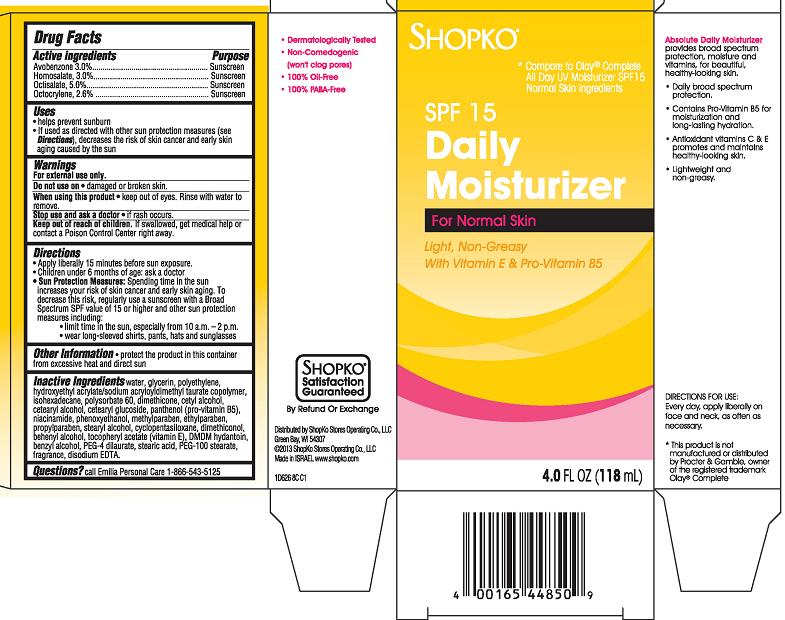 DRUG LABEL: ShopKo Absolute Daily Moisturizing Broad Spectrum SPF15 Sunscreen
NDC: 37012-626 | Form: CREAM
Manufacturer: Shopko Stores Operating Co., LLC
Category: otc | Type: HUMAN OTC DRUG LABEL
Date: 20130506

ACTIVE INGREDIENTS: AVOBENZONE 3 mg/100 mL; HOMOSALATE 3 mg/100 mL; OCTINOXATE 5 mg/100 mL; OCTOCRYLENE 2.6 mg/100 mL
INACTIVE INGREDIENTS: WATER; GLYCERIN; HIGH DENSITY POLYETHYLENE; HYDROXYETHYL ACRYLATE/SODIUM ACRYLOYLDIMETHYL TAURATE COPOLYMER (45000 MPA.S AT 1%); ISOHEXADECANE; POLYSORBATE 60; DIMETHICONE; CETYL ALCOHOL; CETOSTEARYL ALCOHOL; CETEARYL GLUCOSIDE; PANTHENOL; NIACINAMIDE; PHENOXYETHANOL; METHYLPARABEN; ETHYLPARABEN; PROPYLPARABEN; STEARYL ALCOHOL; CYCLOMETHICONE 5; DIMETHICONOL (100000 CST); DOCOSANOL; .ALPHA.-TOCOPHEROL ACETATE; DMDM HYDANTOIN; BENZYL ALCOHOL; PEG-4 DILAURATE; STEARIC ACID; PEG-100 STEARATE; EDETATE DISODIUM

SHOPKO SPF15 Daily Moisturizer For Normal Skin

Active ingredient

Avobenzone 3.0%

Homosalate 3.0%

Oclisalate 5.0%

Octocrylene 2.6%

Purpose

Sunscreen

Uses

- helps prevent sunburn
- If used as directed with other sun protection measures (see Directions), decreases the risk of skin cancer and early skin aging caused by the sun

Warnings

For external use only.

Do not use on

- damaged or broken skin.

When using this product

- keep out of eyes. Rinse with water to remove.

Stop use and ask a doctor

- if rash occurs.

Keep Out of Reach of Children.

If swallowed, get medical help or contact a Poison Control Center right away.

Directions

- Apply liberally 15 minutes before sun exposure.
- Children under 6 months of age: ask a doctor
- Sun Protection Measures: Spending time in the sun increases your risk of skin cancer and early skin aging. To decrease this risk, regularly use a sunscreen with a Broad Spectrum SPF value of 15 or higher and other sun protection measures including:
  - limit time in the sun, especially from 10 a.m. - 2 p.m.
  - wear long-sleeved shirts, pants, hats and sunglasses

Other Information

- protect the product in this container from excessive heat and direct sun

Inactive Ingredients

water, glycerin, polyethylene, hydroxyethyl acrylate/sodium acryloyldimethyl taurate copolymer, isohexadecane, polysorbate 60, dimethicone, cetyl alcohol, cetearyl alcohol, cetearyl glucoside, panthenol (pro-vitamin B5), niacinamide, phenoxythanol, methylparaben, ethylparaben, propylparaben, stearyl alcohol, cyclopentasiloxane, dimethiconol, behenyl alcohol, tocopheryl acetate (vitamin E), DMDM hydantoin, benzyl alcohol, PEG-4 dilaurate, stearic acid, PEG-100 stearate, fragrance, disodium EDTA

Package/Label Principal Display Panel - Carton Label

Shopko*

*Compare to Olay® Complete All Day UV Moisturizer SPF15 Normal Skin Ingredients

SPF 15 Daily Moisturizer For Normal Skin
Light, Non-Greasy
With Vitamin E & Pro-Vitamin B5

- Dermatologically Tested
- Non-Comedogenic (won't clog pores)
- 100% Oil-Free
- 100% PABA-Free

Absolute Daily Moisturizer provides broad spectrum protection, moisture and vitamins, for beautiful, health-looking skin.

- Daily broad spectrum protection.
- Contains Pro-Vitamin B5 for moisturization and long-lasting hydration.
- Antioxidant vitamins C & E promotes and maintains healthy-looking skin.
- Lightweight and non-greasy.

DIRECTIONS FOR USE: Every day, apply liberally on face and neck, as often as necessary.

*This product is not manufactured or distributed by Procter & Gamble, owner of the registered trademark Olay® Complete

4 FL OZ (118 mL)

Distributed by ShopKo Stores Operating Co., LLC
Green Bay, WI 54307
© 2013 ShopKo Stores Operating Co., LLC
Made in Israel. www.shopko.com

1D626 8C C1

Carton Label